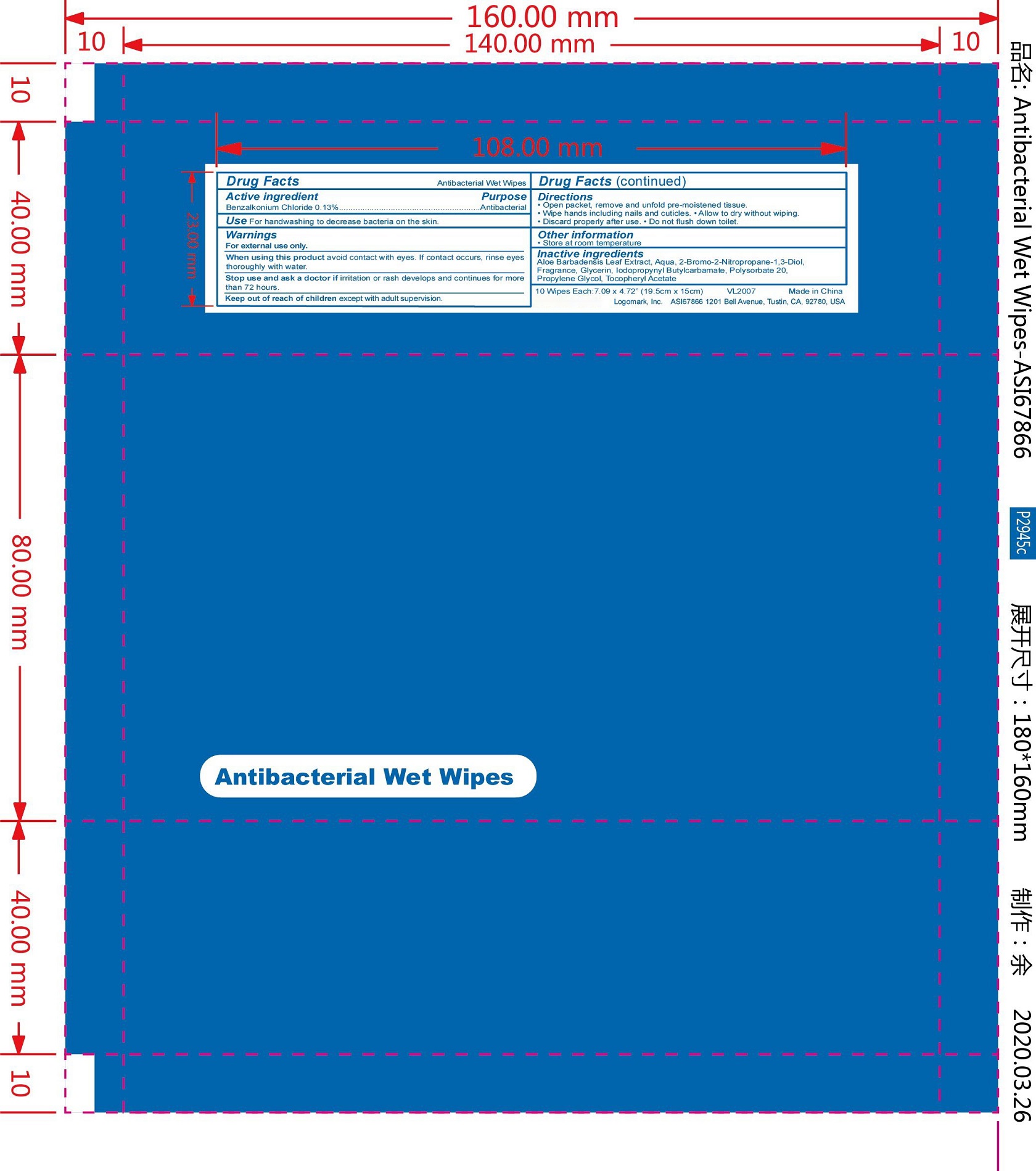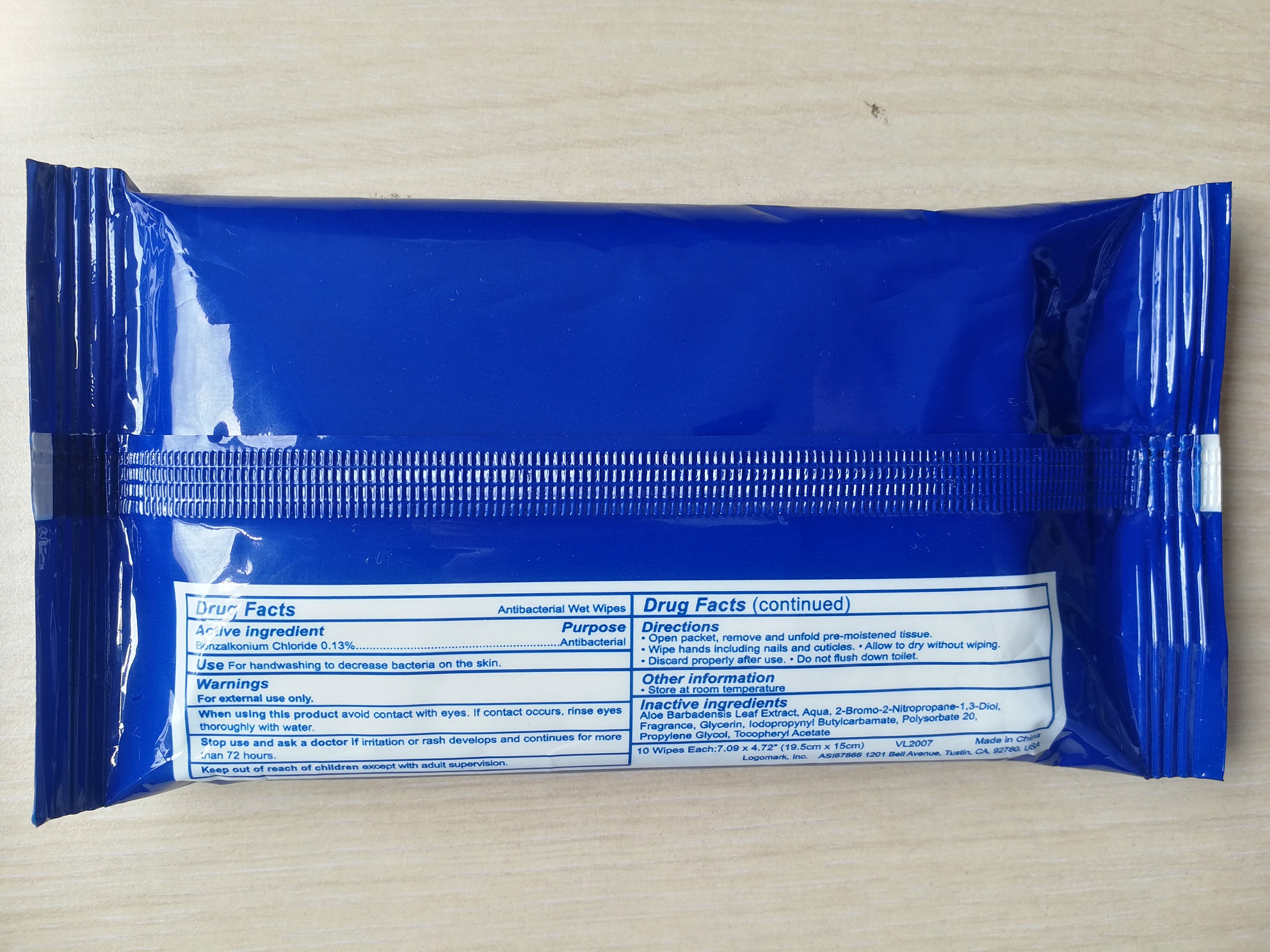 DRUG LABEL: Antibacterial Wet Wipes
NDC: 76635-004 | Form: CLOTH
Manufacturer: Hangzhou Glamcos Biotech CO.,LTD
Category: otc | Type: HUMAN OTC DRUG LABEL
Date: 20231123

ACTIVE INGREDIENTS: BENZALKONIUM CHLORIDE 0.13 g/100 g
INACTIVE INGREDIENTS: IODOPROPYNYL BUTYLCARBAMATE; POLYSORBATE 20; GLYCERIN; WATER; BRONOPOL; ALOE VERA LEAF; PROPYLENE GLYCOL; .ALPHA.-TOCOPHEROL ACETATE, DL-; FRAGRANCE LAVENDER & CHIA F-153480

Drug Facts

Active Ingredient(s)

Benzalkonium Chloride 0.13%

Purpose

Antibacterial

Use

For hand washing to decrease bacteria on the skin.

Warnings

For external use only.

When using this product avoid contact with eyes.If contact occurs,rinse eyes thoroughly with water.

Stop use and ask a doctor if irritation or rash develops and continues for more than 72 hours.

Keep out of reach of children except with adult supervision.

Directions

Open packet,remove and unfold pre-moistened tissue.
Wipe hand including nails and cuticles
Allow to dry without wiping.
Discard properly after use.
Do not flush down toilet.

Other information

Store at room temperature.

Inactive ingredients

Aloe barbadensis leaf extract，Aqua，2-Bromo-2-Nitropropane-1,3-Diol，Fragrance，Glycerin，IodopropynylButylcarbamate，Polysorbate 20，Propylene Glycol，Tocopheryl Acetate